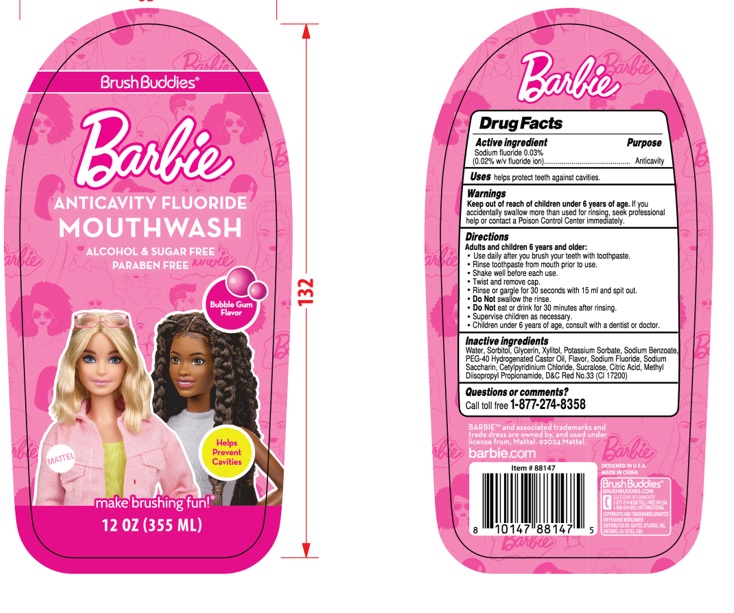 DRUG LABEL: BRUSH BUDDIES BARBIE ANTICAVITY FLUORIDE BUBBLEGUM
NDC: 73928-020 | Form: LIQUID
Manufacturer: Kingkey MBC Life Technology Group co., LTD.
Category: otc | Type: HUMAN OTC DRUG LABEL
Date: 20251009

ACTIVE INGREDIENTS: SODIUM FLUORIDE 0.03 g/100 mL
INACTIVE INGREDIENTS: WATER; SORBITOL; GLYCERIN; XYLITOL; POTASSIUM SORBATE; SODIUM BENZOATE; POLYOXYL 40 HYDROGENATED CASTOR OIL; SACCHARIN SODIUM; CETYLPYRIDINIUM CHLORIDE; SUCRALOSE; CITRIC ACID MONOHYDRATE; METHYL DIISOPROPYL PROPIONAMIDE; D&C RED NO. 33

Active ingredient

SODIUM FLUORIDE 0.03%

Purpose

Anticavity

Uses

helps protect teeth against cavities

Warnings

Keep out of reach of children under 6 years of age. lf you accidentally swallow more than used for rinsing, seek professional help or contact a Poison Control Center immediately.

Directions

Adults and children 6 years and older:

- Use daily after you brush your teeth with toothpaste
- Rinse toothpaste from mouth prior to use.
- Shake well before each use.Twist and remove cap.
- Rinse or gargle for 30 seconds with 15 ml and spit out.
- Do Notswallow the rinse.
- Do Noteat or drink for 30 minutes after rinsing
- Supervise children as necessary.
- Children under 6 years of age, consult with a dentist or doctor.

Inactive ingredients

Water, SORBITOL, GLYCERIN, XYLITOL, POTASSIUM SORBATE, SODIUM BENZOATE, PEG-40 HYDROGENATED CASTOR OIL, FLAVOR
SODIUM FLUORIDE, SODIUM SACCHARIN, CETYLPYRIDINIUM CHLORIDE, SUCRALOSE, CITRIC ACID, METHYL DIISOPROPYL PROPIONAMIDE
D&C Red No.33（CI 17200）

Questions or comments?

Call toll free 1-877-274-8358